DRUG LABEL: Unknown
Manufacturer: Taro Pharmaceuticals U.S.A., Inc.
Category: prescription | Type: HUMAN PRESCRIPTION DRUG LABEL
Date: 20080915

Sterile Water for Injection, USP

Rx Only

Plastic Ampule

DESCRIPTION

This preparation is designed solely for parenteral use only after addition of drugs that require dilution or must be dissolved in an aqueous vehicle prior to injection.

Sterile Water for Injection, USP is a sterile, nonpyrogenic preparation of water for injection, which contains no bacteriostat, antimicrobial agent or added buffer and is supplied only in single-dose containers to dilute or dissolve drugs for injection. The blow-fill-sealed twist-off top, plastic ampule is molded from a specially formulated polypropylene. For I.V. injection, add sufficient amount to a solute to make an approximately isotonic solution.

Water for Injection, USP is chemically designated H2O. The pH is 5.0 to 7.0.

CLINICAL PHARMACOLOGY

Water is an essential constituent of all body tissues and accounts for approximately 70% of total body weight. Average normal adult daily requirement ranges from two to three liters (1.0 to 1.5 liters each for insensible water loss by perspiration and urine production).

Water balance is maintained by various regulatory mechanisms. Water distribution depends primarily on the concentration of electrolytes in the body compartments and sodium (Na^+) plays a major role in maintaining physiologic equilibrium.

The small volume of fluid provided by Sterile Water for Injection, USP when used only as a pharmaceutic aid for diluting or dissolving drugs for parenteral injection, is unlikely to exert a significant effect on fluid balance except possibly in newborns or very small infants.

INDICATIONS AND USAGE

This preparation is indicated only for diluting or dissolving drugs intended for parenteral injection, according to instructions of the manufacturer of the drug to be administered.

CONTRAINDICATIONS

Sterile Water for Injection, USP must be made approximately isotonic prior to use.

WARNINGS

Intravenous administration of Sterile Water for Injection without a solute may result in hemolysis.

Some drugs for injection may be incompatible in a given vehicle, or when combined in the same vehicle. Consult with pharmacist, if available.

The plastic ampule is molded from a specially formulated polypropylene.

When diluting or dissolving drugs, mix thoroughly and use promptly.

Do not store reconstituted solutions of drugs for injection unless otherwise directed by the manufacturer of the solute.

PRECAUTIONS

Do not use unless the solution is clear and seal intact. Do not reuse single-dose containers, discard unused portion.

Consult the manufacturer's instructions for choice of vehicle, appropriate dilution or volume for dissolving the drugs to be injected, including the route and rate of injection.

Inspect reconstituted (diluted or dissolved) drugs for clarity (if soluble) and freedom from unexpected precipitation or discoloration prior to administration.

Pregnancy Category C

Animal reproduction studies have not been conducted with Sterile Water for Injection, USP. It is also not known whether Sterile Water for Injection, USP can cause fetal harm when administered to a pregnant woman or can affect reproduction capacity. Sterile Water for Injection, USP with additives should be given to a pregnant woman only if clearly needed.

Carcinogenesis, Mutagenesis, Impairment of Fertility

Studies with solutions in polypropylene ampules have not been performed to evaluate carcinogenic potential, mutagenic potential or effects on fertility.

Drug Interactions

Some drugs for injection may be incompatible in a given vehicle, or when combined in the same vehicle. Consult with pharmacist, if available.

When diluting or dissolving drugs, mix thoroughly and use promptly.

Do not store reconstituted solutions of drugs for injection unless otherwise directed by the manufacturer of the solute.

Do not use unless the solution is clear and seal intact. Do not reuse single-dose containers. Discard unused portion

ADVERSE REACTIONS

Reactions which may occur because of this solution, added drugs or the technique of reconstitution or administration include febrile response, local tenderness, abscess, tissue necrosis or infection at the site of injection, venous thrombosis or phlebitis extending from the site of injection and extravasation.

If an adverse reaction does occur, evaluate the patient, institute appropriate countermeasures, and if possible, retrieve and save the remainder of the unused vehicle for examination.

OVERDOSAGE

Use only as a diluent or solvent. This parenteral preparation is unlikely to pose a threat of fluid overload except possibly in newborn or very small infants.

DOSAGE AND ADMINISTRATION

The volume of the preparation to be used for diluting or dissolving any drug for injection, is dependent on the vehicle concentration, dose and route of administration as recommended by the manufacturer of the drug and be administered.

Use aseptic technique for entry and withdrawal from container.

This parenteral should be inspected visually for particulate matter and discoloration prior to administration, whenever solution and container permit. See PRECAUTIONS.

HOW SUPPLIED

NDC # | Volume
51672-3018-5 | single-dose 5 mL Ampule
51672-3018-3 | single-dose 10 mL Ampule

Packaged in a polypropylene ampule. Ampules are packaged 20 per tray.

STORAGE AND HANDLING

Store at 20°-25°C (68°-77°F) [see USP Controlled Room Temperature].

Mfd. by: Taro Pharmaceuticals Ireland, Ltd., Roscrea, Co. Tipperary, Ireland
Dist. by: Taro Pharmaceuticals U.S.A., Inc., Hawthorne, NY 10532